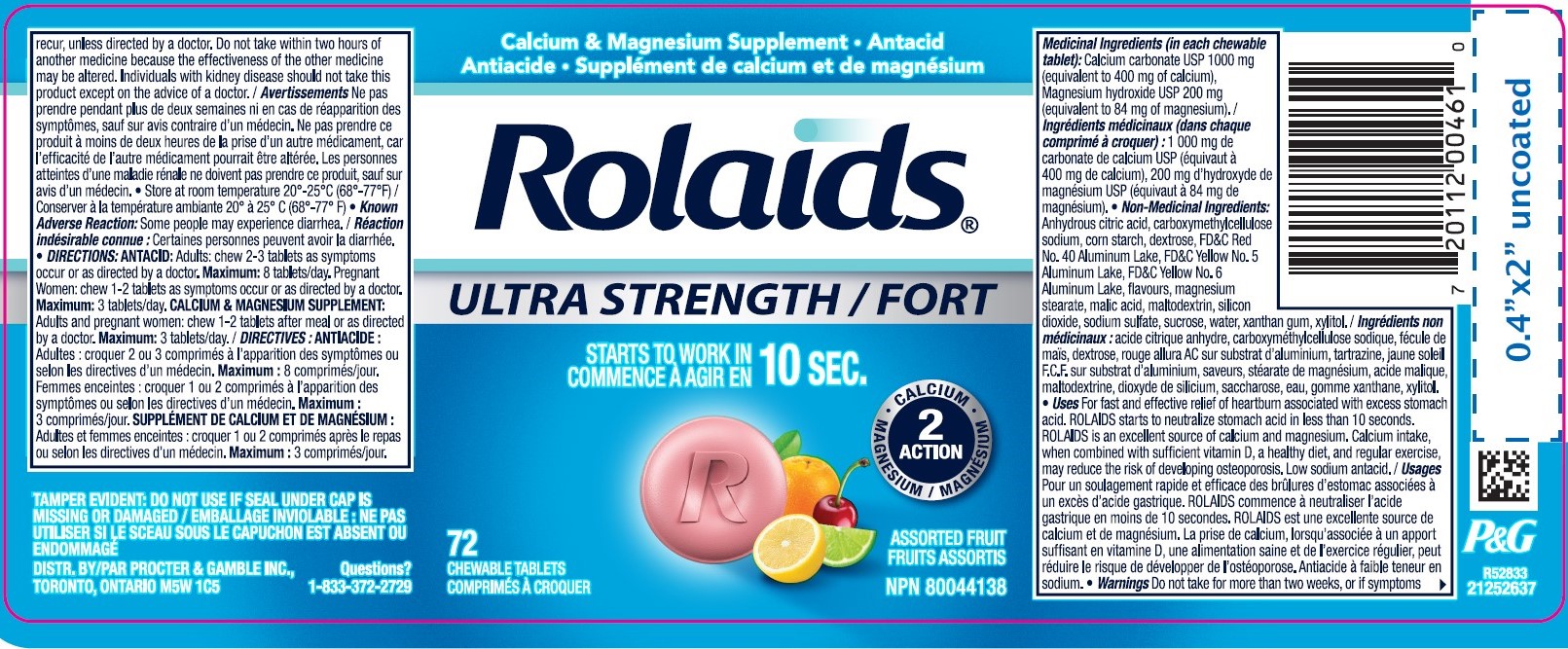 DRUG LABEL: Calcium Carbonate, Magnesium Hydroxide
NDC: 10267-0041 | Form: TABLET, CHEWABLE
Manufacturer: Contract Pharmacal Corp.
Category: otc | Type: HUMAN OTC DRUG LABEL
Date: 20250616

ACTIVE INGREDIENTS: MAGNESIUM HYDROXIDE 200 mg/1 1; CALCIUM CARBONATE 1000 mg/1 1
INACTIVE INGREDIENTS: FD&C YELLOW NO. 6 ALUMINUM LAKE; PROPYLENE GLYCOL; MALIC ACID; MALTODEXTRIN; SORBITOL; XANTHAN GUM; SILICON DIOXIDE; DEXTROSE; .ALPHA.-TOCOPHEROL, DL-; SODIUM SULFATE; ANHYDROUS CITRIC ACID; ACACIA; STARCH, CORN; FD&C YELLOW NO. 5 ALUMINUM LAKE; MAGNESIUM STEARATE; FD&C RED NO. 40; BENZYL ALCOHOL; PROPYLENE GLYCOL ALGINATE; CARBOXYMETHYLCELLULOSE; SUCROSE; XYLITOL

5758- Export